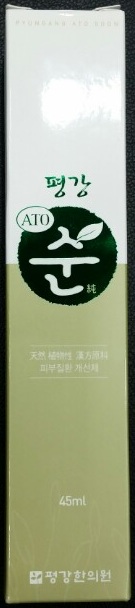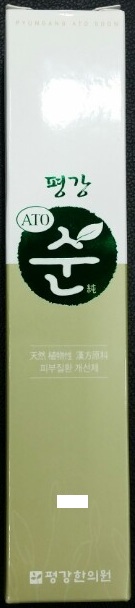 DRUG LABEL: PYUNG GANG ATO SOON
NDC: 69698-2001 | Form: CREAM
Manufacturer: Pyung Gang Oriental Medical Clinic
Category: otc | Type: HUMAN OTC DRUG LABEL
Date: 20170904

ACTIVE INGREDIENTS: MINERAL OIL 0.45 g/45 mL
INACTIVE INGREDIENTS: CNIDIUM ROOT; DIGITALIS PURPUREA WHOLE; PAEONIA LACTIFLORA ROOT; FU LING; LYCIUM CHINENSE FRUIT; ASTRAGALUS PROPINQUUS ROOT; LEMNA MINOR; ALLIUM FISTULOSUM BULB; WHITE MULBERRY; HOUTTUYNIA CORDATA FLOWERING TOP; SAURURUS CHINENSIS WHOLE; PINE NEEDLE OIL (PINUS SYLVESTRIS); ANGELICA ATROPURPUREA ROOT; DIOSCOREA VILLOSA ROOT; ELM

ACTIVE INGREDIENTS

Mineral Oil 1%

PURPOSE

Skin Protectant

DIRECTION

Apply to affected area twice daily, morning and evening. Shake the bottle before use.

WARNING

- Keep product out of direct sunlight, high temperature and humidity.
- Store in a cool dry place.
- Be careful not to get it in your eyes.

KEEP OUT OF REACH OF CHILDREN

USES

To help the treatment of atopy, psoriasis and sensitive dermatitis.

INACTIVE INGREDIENT

Elm, Eoseongcho, Houttuynia, Pine needles, Korean angelica root, cnidium, foxglove, Peony, Poria cocos, Yam, Matrimony vine, Milk vetch root, Duckweed, Green onion, Mulberry.

OTHER INFORMATION

- Any items past the expiration date or damaged in transit can be exchanged where you originally purchased the item.
- It is even better the effect with avoiding instant food, flour foods, fast food, carbonated drink, alcohol and chemicals are added processed foods.

SPL UNCLASSIFIED SECTION

CAUTION:

To assure freshness and potency, store at room temperature 15oC - 30oC.

Store away from heat, light and moisture.